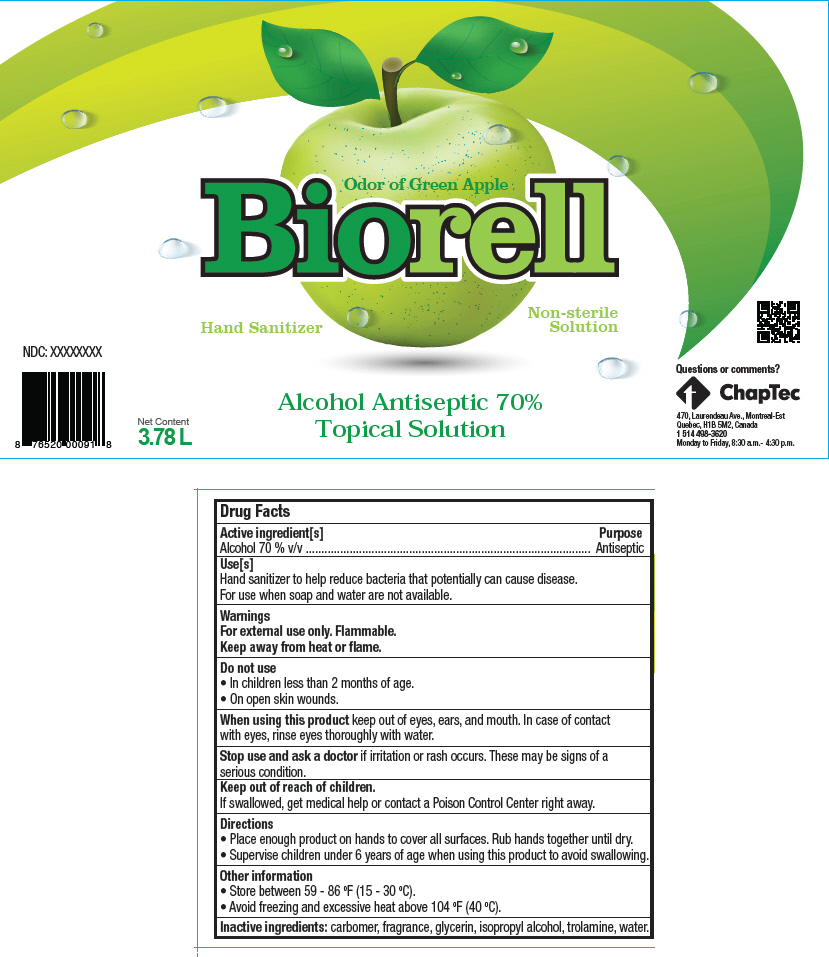 DRUG LABEL: Biorell
NDC: 79738-001 | Form: GEL
Manufacturer: Chaptec Inc
Category: otc | Type: HUMAN OTC DRUG LABEL
Date: 20200911

ACTIVE INGREDIENTS: ALCOHOL 70 mL/100 mL
INACTIVE INGREDIENTS: CARBOMER HOMOPOLYMER, UNSPECIFIED TYPE; Glycerin; Isopropyl alcohol; Trolamine; Water

Biorell

Drug Facts

Active ingredient[s]

Alcohol 70 % v/v

Purpose

Antiseptic

Use[s]

Hand sanitizer to help reduce bacteria that potentially can cause disease.

For use when soap and water are not available.

Warnings

For external use only. Flammable.

Keep away from heat or flame.

Do not use

- In children less than 2 months of age.
- On open skin wounds.

When using this product keep out of eyes, ears, and mouth. In case of contact with eyes, rinse eyes thoroughly with water.

Stop use and ask a doctor if irritation or rash occurs. These may be signs of a serious condition.

Keep out of reach of children.

If swallowed, get medical help or contact a Poison Control Center right away.

Directions

- Place enough product on hands to cover all surfaces. Rub hands together until dry.
- Supervise children under 6 years of age when using this product to avoid swallowing.

Other information

- Store between 59 - 86 °F (15 - 30 °C).
- Avoid freezing and excessive heat above 104 °F (40 °C).

Inactive ingredients

carbomer, fragrance, glycerin, isopropyl alcohol, trolamine, water.

Questions or comments?

1 514 498-3620

Monday to Friday, 8:30 a.m.- 4:30 p.m.

PRINCIPAL DISPLAY PANEL - 3.78 L Bottle Label

Odor of Green Apple
Biorell

Hand Sanitizer

Non-sterile
Solution

Alcohol Antiseptic 70%
Topical Solution

Net Content
3.78 L